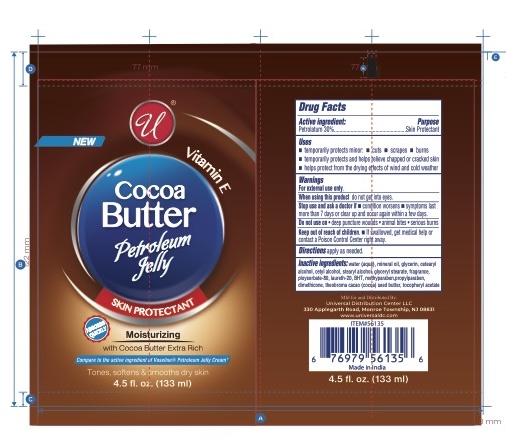 DRUG LABEL: COCOA BUTTER PETROLEUM jelly
NDC: 83650-104 | Form: CREAM
Manufacturer: Savvy Care & Cosmetics Pvt. Ltd.
Category: otc | Type: HUMAN OTC DRUG LABEL
Date: 20250709

ACTIVE INGREDIENTS: PETROLATUM 30 g/100 mL
INACTIVE INGREDIENTS: WATER; MINERAL OIL; GLYCERIN; CETOSTEARYL ALCOHOL; CETYL ALCOHOL; STEARYL ALCOHOL; GLYCERYL MONOSTEARATE; POLYSORBATE 80; LAURETH-20; BUTYLATED HYDROXYTOLUENE; METHYLPARABEN; PROPYLPARABEN; DIMETHICONE, UNSPECIFIED; TOCOPHEROL

Cocoa Butter Petroleum Jelly

Active ingredient:

Petrolatum 30%

Purpose

Skin Protectant

Uses

• temporarily protects minor: • cuts • scrapes • burns
• temporarily protects and helps relieve chapped or cracked skin
• helps protect from the drying effects of wind and cold weather

Warnings

For external use only.

When using this productdo not get into eyes.

Stop use and ask a doctor if• condition worsens • symptoms last more than 7 days or clear up and occur again within a few days.

Do not use on• deep puncture wounds • animal bites • serious burns

Keep out of reach of children.• If swallowed, get medical help or contact a Poison Control Center right away.

Directions

apply as needed.

Inactive ingredients:

water (aqua), mineral oil, glycerin, cetearyl alcohol, cetyl alcohol, stearyl alcohol, glyceryl stearate, fragrance, polysorbate 80, laureth-20, BHT, methylparaben, propylparaben, dimethicone, tocopherol.

New

Vitamin E

Moisturizing

with Cocoa Butter Extra Rich

Compare to the active ingredient of Vaseline®Petroleum Jelly Cream*

Tones, softens & smooths dry skin